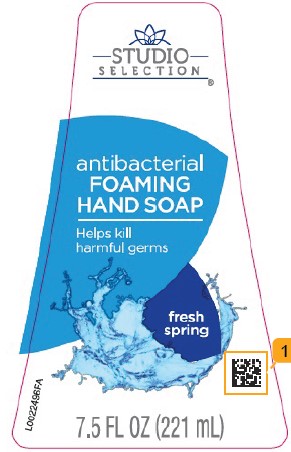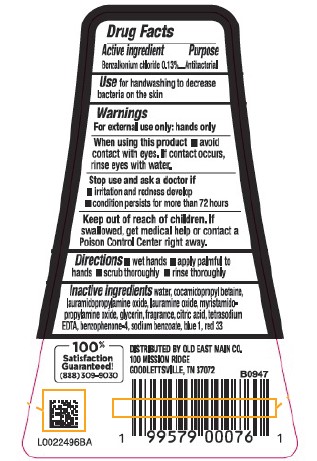 DRUG LABEL: Hand Wash
NDC: 55910-628 | Form: LIQUID
Manufacturer: Old East Main Co.
Category: otc | Type: HUMAN OTC DRUG LABEL
Date: 20260302

ACTIVE INGREDIENTS: BENZALKONIUM CHLORIDE 1.3 mg/1 mL
INACTIVE INGREDIENTS: WATER; COCAMIDOPROPYL BETAINE; LAURAMIDOPROPYLAMINE OXIDE; LAURAMINE OXIDE; MYRISTAMIDOPROPYLAMINE OXIDE; GLYCERIN; CITRIC ACID MONOHYDRATE; EDETATE SODIUM; SULISOBENZONE; SODIUM BENZOATE; FD&C BLUE NO. 1; D&C RED NO. 33

Studio Selection 628.002/628AF
Antibacterial Hand Soap

Active ingredient

Benzalkonium chloride 0.13%

purpose

Antibacterial

Use

for handwashing to decrease bacteria on the skin

Warnings

For external use only: hands only

When using this product

- avoid contact with eyes. If contact occurs, rinse eyes thoroughly with water.

Stop use and ask a doctor if

- irritation and redness develop
- condition persists for more than 72 hours

Keep out of reach of children.

If swallowed, get medical help or contact a Poison Control Center right away.

Directions

- wet hands
- apply palmful to hands
- scrub thoroughly
- rinse thoroughly

Inactive ingredients

water, cocamidopropyl betaine, lauramidopropylamine oxide, lauramine oxide, myristamidopropylamine oxide, glycerin, fragrance, citric acid, tetrasodium EDTA, benzophenone-4, sodium benzoate, blue 1, red 33

ADVERSE REACTION

DISTRIBUTED BY OLD EAST MAIN C0

100 MISSION RIDGE

GOODLETTSVILLE, TN 37072

100% SATISFATION GUARANTEED (888)309-9030

principal display panel

Studio Selection®

antibacterial

FOAMING HAND SOAP

Helps kill harmful germs

fresh spring

7.5 FL OZ (221 mL)